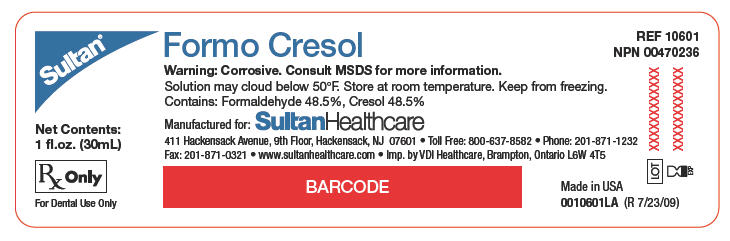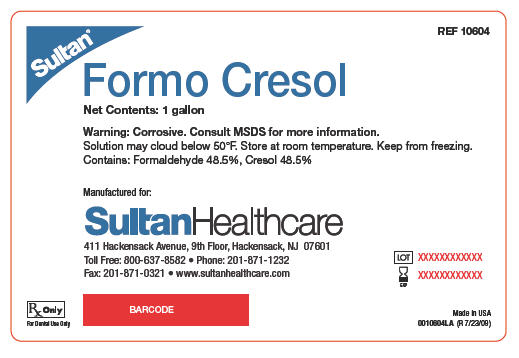 DRUG LABEL: Formo Cresol
NDC: 0699-0001 | Form: LIQUID
Manufacturer: DSHealthcare
Category: prescription | Type: HUMAN PRESCRIPTION DRUG LABEL
Date: 20100204

ACTIVE INGREDIENTS: Cresol 485 mg/1 g
INACTIVE INGREDIENTS: Glycerin

Formocresol/Buckley's Formocresol

DIRECTIONS FOR USE

REF – 10606 – Formocresol – 1oz/30mL
REF – 10203 – Buckley's Formocresol – 1oz/30mL
NPN number: Formocresol – 00470236
NPN number: Buckley's Formocresol - 00470155
For dental use only.
USA: Rx only.

1. DESCRIPTION

Formocresol: 48.5% formaldehyde, 48.5% cresol, 3% glycerine. Buckley's Formocresol: 19% formaldehyde, 35% cresol, 17.5% gylcerine.

2. INDICATIONS

Indicated as a disinfectant and devitalizing solution used as part of endodontic treatment.

3. CONTRAINDICATIONS

This product should not be used with individuals with known sensitivities to formaldehyde or cresol. This product should not be used with individuals who are pregnant or suspected to be pregnant without a prior physician consultation.

4. PRECAUTIONS

This product can cause severe burns of skin and mucosa. Take precautions protect skin, mucosa and eyes during use.

5. WARNINGS

Do not swallow. Do not allow material to come into contact with intact skin or mucosa. Wear eye protection when handling. Ensure proper tooth isolation, including rubber dam when applying. Keep out of reach of children. For professional dental use only.

6. DOSAGE AND ADMINISTRATION

1. Intracanal disinfection in permanent teeth: Isolate the tooth with a rubber dam. Clean, de-bride and instrument the canals. Rinse and dry the canal spaces. Moisten a small cotton pellet with formocresol. Blot or wring any excess liquid from the pellet. Place the cotton pellet in the pulp chamber and seal the access hole with a temporary filling material. Recall the patient after a minimum of 48 hours and remove the pellet. Complete the endodontic treatment and restore.
2. Formocresol pulpotomy in primary teeth: Isolate the tooth with a rubber dam. Remove visible caries. Remove the coronal pulp with an excavator or bur leaving the radicular pulp. Achieve hemostasis. Moisten small cotton pellets with fomocresol. Blot or wring any excess liquid from the pellet. Place the pellets directly on the radicular pulp stumps for 5 minutes. Place a base or a core in the tooth and restore.

7. STORAGE

Store between 59°-86°F (15°-30°C). Protect from freezing.

SultanHealthcare
411 Hackensack Avenue, 9th Floor, Hackensack, NJ 07601
Toll Free: 800-637-8582 • Phone: 201-871-1232
Fax: 201-871-0321 • www.sultanhealthcare.com

Made in the USA
Form #0010601DF (R 7/22/09)

PRINCIPAL DISPLAY PANEL - 30 mL Bottle Label

Sultan®

REF 10601
NPN 00470236

Formo Cresol

Net Contents:
1 fl.oz. (30mL)

Warning: Corrosive. Consult MSDS for more information.
Solution may cloud below 50°F. Store at room temperature. Keep from freezing.
Contains: Formaldehyde 48.5%, Cresol 48.5%

Manufactured for: SultanHealthcare
411 Hackensack Avenue, 9th Floor, Hackensack, NJ 07601 • Toll Free: 800-637-8582 • Phone: 201-871-1232
Fax: 201-871-0321 • www.sultanhealthcare.com • Imp. by VDI Healthcare, Brampton, Ontario L6W 4T5

Rx Only
For Dental Use Only

LOT
EXP

Made in USA
0010601LA (R 7/23/09)

PRINCIPAL DISPLAY PANEL - 1 Gallon Bottle Label

Sultan®

REF 10604

Formo Cresol

Net Contents: 1 gallon

Warning: Corrosive. Consult MSDS for more information.
Solution may cloud below 50°F. Store at room temperature. Keep from freezing.
Contains: Formaldehyde 48.5%, Cresol 48.5%

Manufactured for:
SultanHealthcare
411 Hackensack Avenue, 9th Floor, Hackensack, NJ 07601
Toll Free: 800-637-8582 • Phone: 201-871-1232
Fax: 201-871-0321 • www.sultanhealthcare.com

Rx Only
For Dental Use Only

LOT
EXP

Made in USA
0010604LA (R 7/23/09)